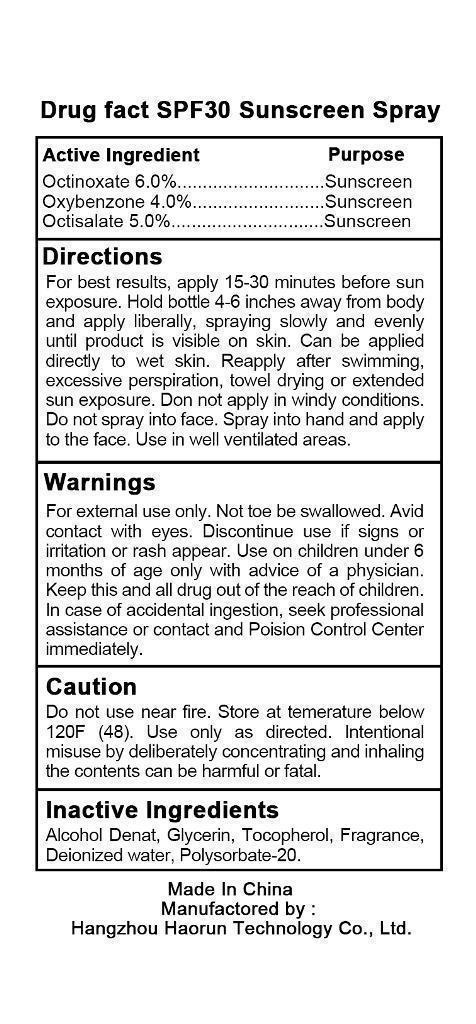 DRUG LABEL: SPF 30 Sunscreen
NDC: 57817-300 | Form: SPRAY
Manufacturer: Hangzhou Haorun Technology CO.,LTD. 
Category: otc | Type: HUMAN OTC DRUG LABEL
Date: 20130330

ACTIVE INGREDIENTS: OCTINOXATE 6 g/100 g; OXYBENZONE 4 g/100 g; OCTISALATE 5 g/100 g
INACTIVE INGREDIENTS: ALCOHOL; Glycerin; Tocopherol; WATER; POLYSORBATE 20

SPF 30 Sunscreen Spray

Active Ingredient

Octinoxate 6.0%

Oxybenzone 4.0%

Octisalate 5.0%

PURPOSE

sunscreen

Use

Protection from the sun’s damaging effects.

Warnings

For external use only.Not to be swallowed.Avid contact with eyes.Discontinue use if signs or irritation or rash appear .Use on children under 6 months of age only with advice of a physician.

KEEP OUT OF REACH OF CHILDREN

Keep this and all drug out of the reach of children.In case of accidental ingestion,seek professional assisitance or contact and Poision Control Center imdediately.

Do not use near fire,Store at temerature below 120F(48).Use only as directed.intentional misuse by deliberately concentrating and inhaling the contents can be harmful or fatal.

Direction

For best results,apply 15-30 minutes befroes sun exposure.Hold bottle 4-6 inches away from body and apply liberally,spraying slowly and evenly until product is visible on skin.Can be applied directly to wet skin.Reapply after swimming,excessive perspiration,towel drying or extended sunexposure .Don not apply in windy conditions.Do not spray into face,Spray into hand and apply to the face.Use in well ventilated areas.

Inactive Ingredient

Alcohal Denat,Glycerin,Tocopherol,Fragrance,Deionized Water,Polysorbate-20